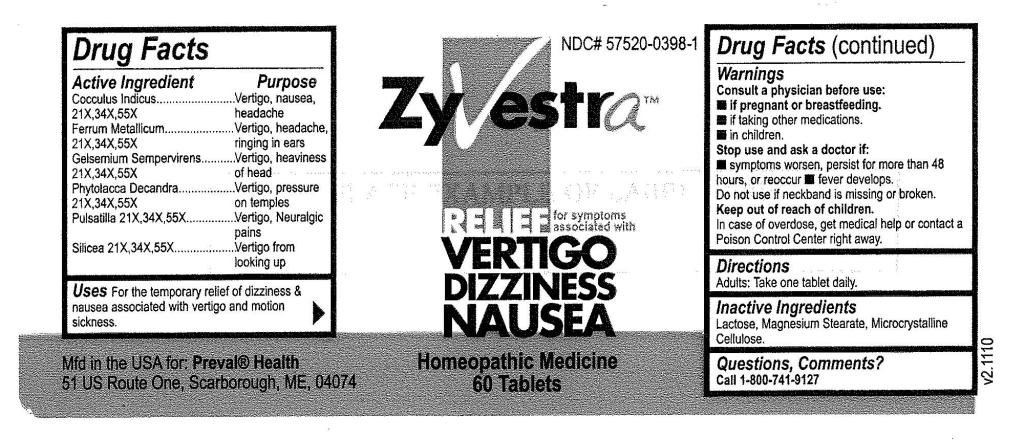 DRUG LABEL: Zyvestra
NDC: 57520-0398 | Form: TABLET
Manufacturer: Apotheca Company
Category: homeopathic | Type: HUMAN OTC DRUG LABEL
Date: 20101203

ACTIVE INGREDIENTS: ANAMIRTA COCCULUS SEED 55 [hp_X]/1 1; IRON 55 [hp_X]/1 1; GELSEMIUM SEMPERVIRENS ROOT 55 [hp_X]/1 1; PHYTOLACCA AMERICANA ROOT 55 [hp_X]/1 1; SILICON DIOXIDE 55 [hp_X]/1 1
INACTIVE INGREDIENTS: CELLULOSE, MICROCRYSTALLINE; LACTOSE; MAGNESIUM STEARATE

Zyvestra

ACTIVE INGREDIENT

ACTIVE INGREDIENTS: Cocculus indicus 21X, 34X, 55X, Ferrum metallicum 21X, 34X, 55X, Gelsemium sempervirens 21X, 34X, 55X, Phytolacca decandra 32X, 34X, 55X, Pulsatilla 21X, 34X, 55X, Silicea 21X, 34X, 55X.

PURPOSE

USES: For the temporary relief of dizziness and nausea associated with vertigo and motion sickness.

WARNINGS: Consult a physician before use:

If pregnant or breastfeeding

if taking other medications

in children.

Stop use and ask a doctor if:

symptoms worse, persist for more that 48 hours, or reoccur

fever develops.

Do not use if neckband is missing or broken.

Keep out of reach of children. In case of overdose, get medical help or contact a Poison Control Center right away.

DOSAGE AND ADMINISTRATION

DIRECTIONS: Adults: Take one tablet daily.

INACTIVE INGREDIENT

INACTIVE INGREDIENTS: Lactose, Magnesium stearate, Microcrystalline cellulose.

KEEP OUT OF REACH OF CHILDREN. In case of overdose, get medical help or contact a Poison Control Center right away.

INDICATIONS AND USAGE

USES: For the temporary relief of dizziness and nausea associated with vertigo and motion sickness.

Questions, Comments?

Call 1-800-741-9127

Mfd in the USA for: PREVAL HEALTH

51 US Route One, Scarborough, ME 04074

PACKAGE LABEL

NDC# 57520-0398-1

ZYVESTRA

RELIEF from symptoms associated with

VERTIGO

DIZZINESS

NAUSEA

Homeopathic Medicine

60 Tablets